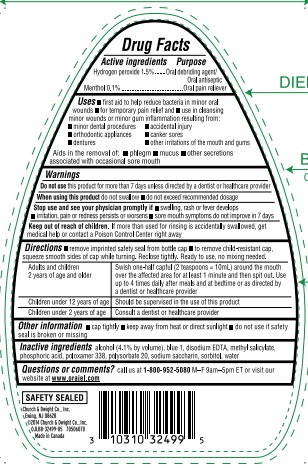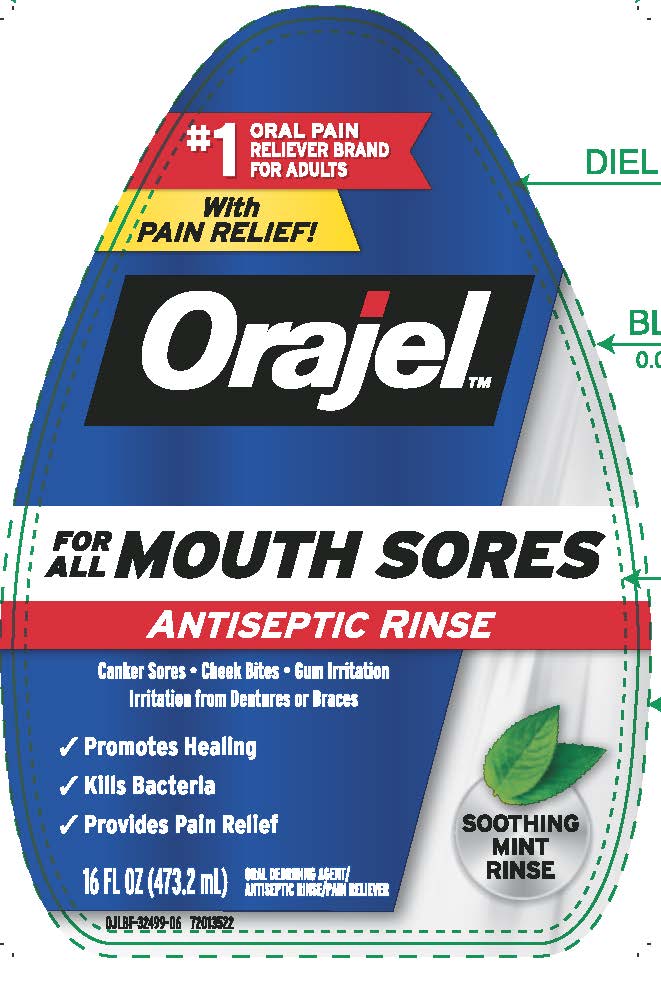 DRUG LABEL: Orajel Antiseptic Rinse For All Mouth Sores
NDC: 10237-760 | Form: LIQUID
Manufacturer: Church & Dwight Co., Inc.
Category: otc | Type: HUMAN OTC DRUG LABEL
Date: 20251212

ACTIVE INGREDIENTS: HYDROGEN PEROXIDE 15 mg/1 mL; MENTHOL, UNSPECIFIED FORM 1 mg/1 mL
INACTIVE INGREDIENTS: FD&C BLUE NO. 1; EDETATE DISODIUM; METHYL SALICYLATE; PHOSPHORIC ACID; POLOXAMER 338; POLYSORBATE 20; SACCHARIN SODIUM; SORBITOL; WATER; ALCOHOL

Orajel Antiseptic Rinse for All Mouth Sores

ACTIVE INGREDIENT

Hydrogen peroxide 1.5%

Menthol 0.1%

PURPOSE

Oral debriding agent/Oral antiseptic

Oral pain reliever

INDICATIONS AND USAGE

- first aid to help reduce bacteria in minor oral wounds
- for temporary pain relief and
- use in cleansing minor wounds or minor gum inflammation resulting from:
- minor dental procedures
- accidental injury
- orthodontic appliances
- canker sores
- dentures
- other irritations of the mouth and gums

Aids in the removal of:

- phlegm
- mucus
- other secretions associated with occasional sore mouth

WARNINGS

When using this productdo not swallow

do not exceed recommended dosage

DO NOT USE

Do not usethis product for more than 7 days unless directed by a dentist or healthcare provider

Stop use and see your physician promptly ifswallowing, rash or fever develops; irritation, pain or redness persists or worsens; sore mouth symptoms do not improve in 7 days

Keep out of reach of children.If more than used for rinsing is accidentally swallowed, get medical help or contact a Poison Control Center right away

Directions

- remove imprinted safety seal from bottle cap
- to remove child-resistant cap, squeeze smooth sides of cap while turning. Reclose tightly. Ready to use, no mixing needed.

Adults and children; 2 years of age and older |  |  | Swish one-half capful (2 tesapoons=10mL) around the mouth over the affected area for at least 1 minute and then spit out. Use up to 4 times daily after meals and at bedtime or as directed by a dentist or healthcare provider
Children under 12 years of age |  |  | Should be supervised in the use of this product
Children under 2 years of age |  |  | Consult a dentist or healthcare provider

Other Information

- cap tightly
- keep away from heat or direct sunlight
- do not use if safety seal is broken or missing

INACTIVE INGREDIENT

alcohol (4.1% by volume), blue 1, disodium EDTA, methyl salicylate, phosphoric acid, poloxamer 338, polysorbate 20, sodium saccharin, sorbitol, water

QUESTIONS

Questions or commentscall us at 1–800–952–5080 M–F 9am–5pm ET or visit our website atwww.orajel.com

PACKAGE LABEL

#1

ORAL PAIN

RELIEVER BRAND

FOR ADULTS

With

PAIN RELIEF!

Orajel™

FOR ALL MOUTH SORES

ANTISEPTIC RINSE

Canker Sores Cheek Bites Gum Irritation

Irritation from Dentures or Braces

Promotes Healing

Kills Bacteria

Provides Pain Relief

SOOTHING

MINT

RINSE

ORAL DEBRIDING AGENT / ANTISEPTIC RINSE / PAIN RELIEVER

16 FL OZ (473.2 mL)